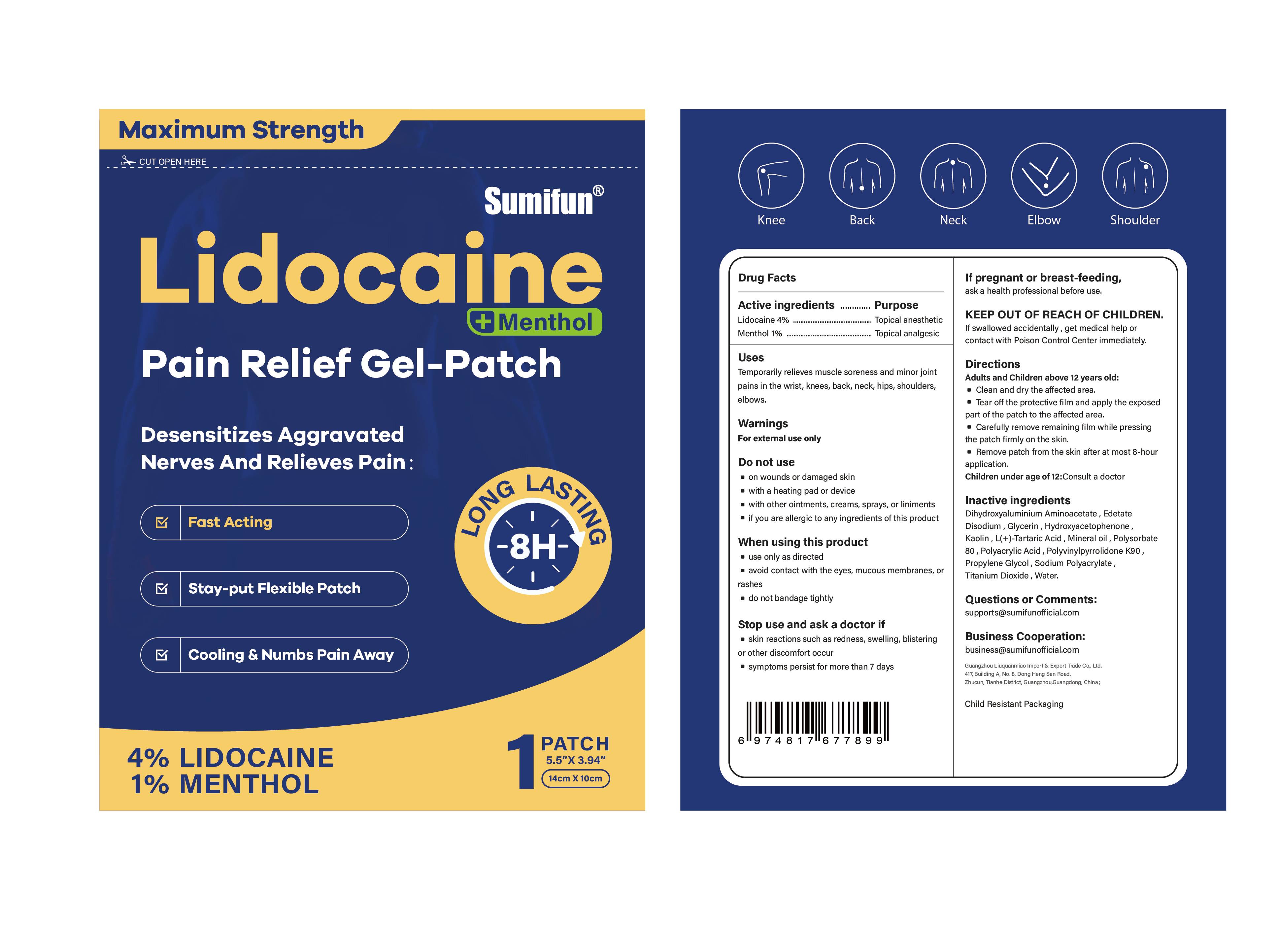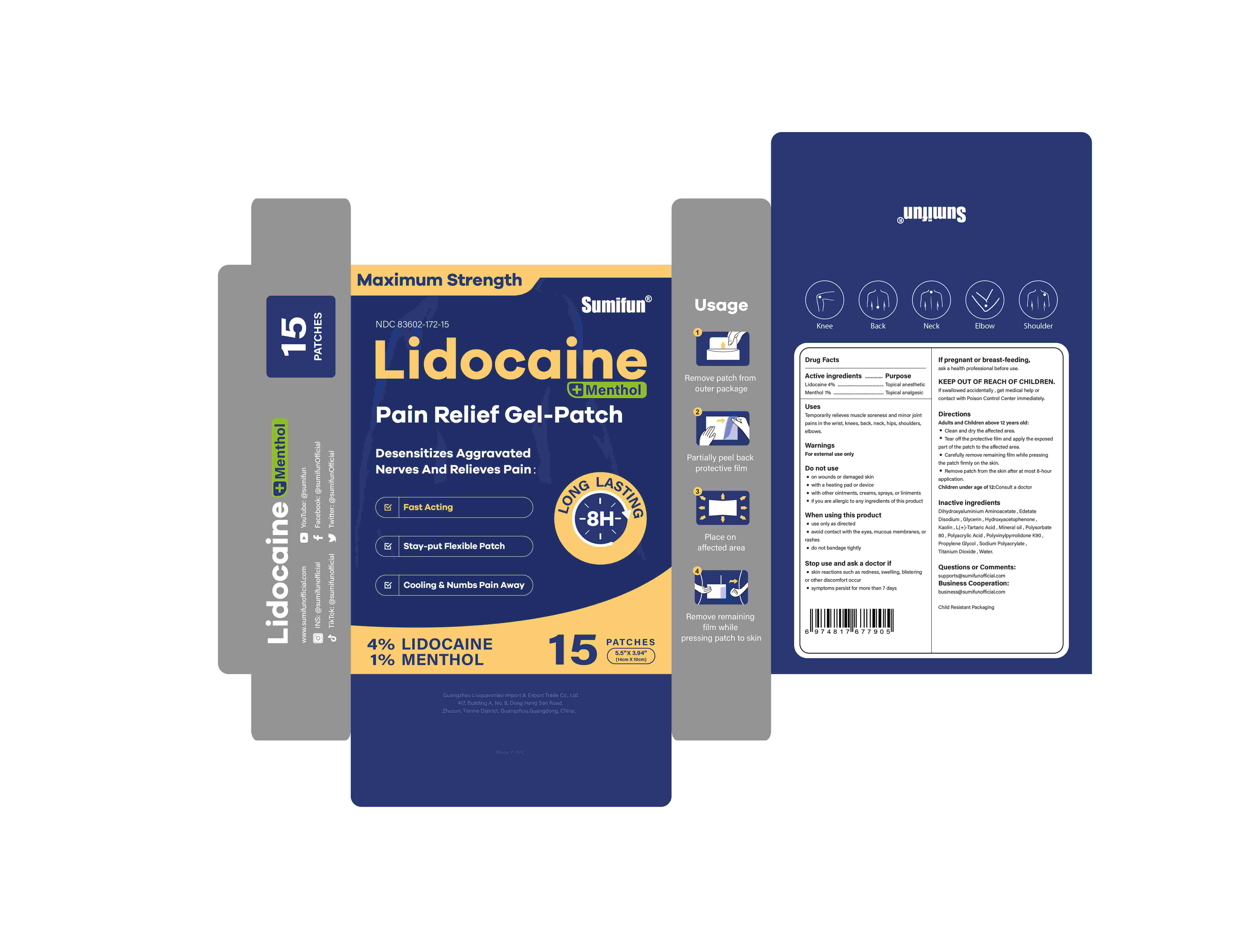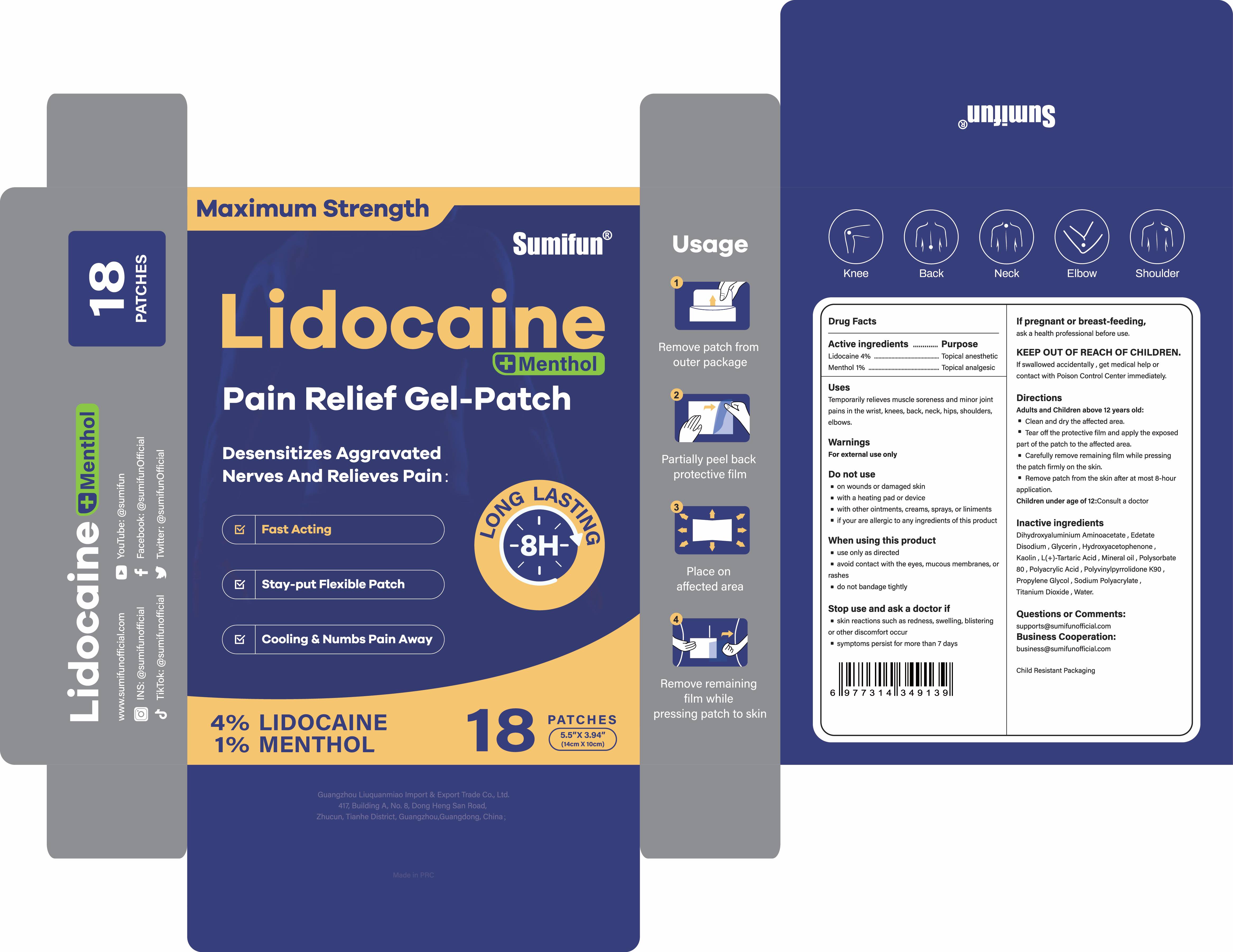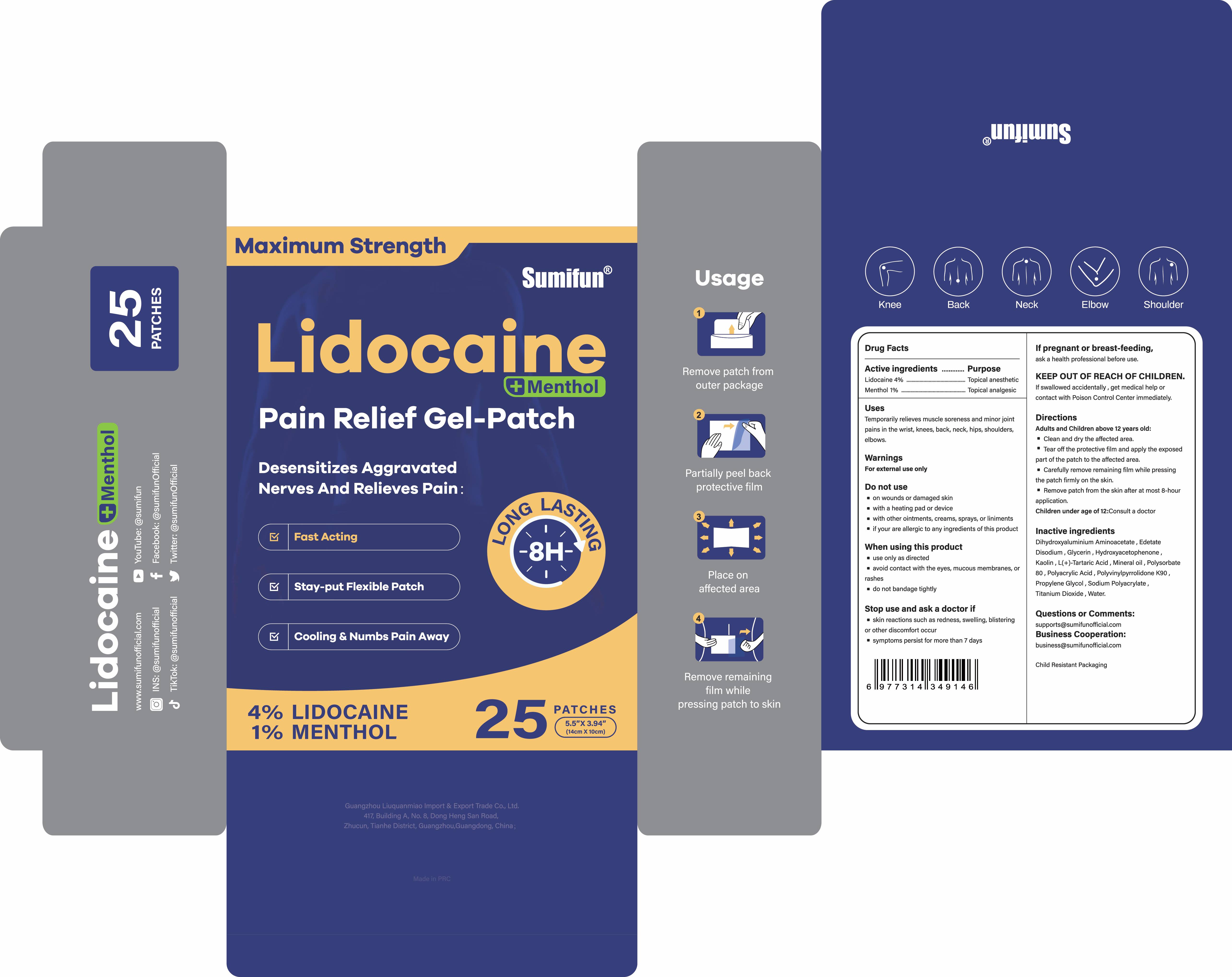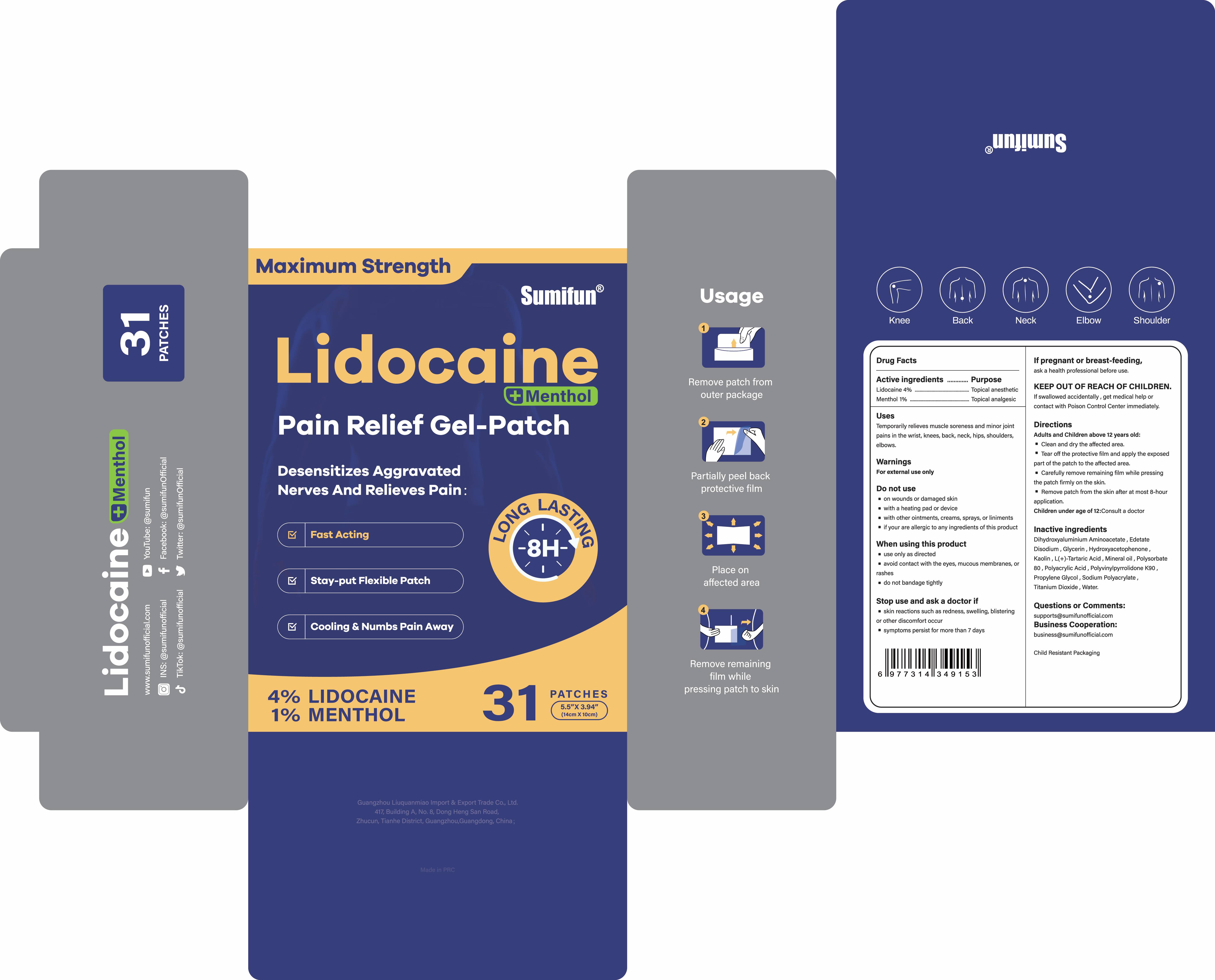 DRUG LABEL: Pain Relief Gel-Patch
NDC: 83602-172 | Form: PATCH
Manufacturer: Guangzhou Liuquanmiao Import & Export Trade Co., Ltd.
Category: otc | Type: HUMAN OTC DRUG LABEL
Date: 20250702

ACTIVE INGREDIENTS: LIDOCAINE 0.04 g/1 g; MENTHOL 0.01 g/1 g
INACTIVE INGREDIENTS: KAOLIN; TARTARIC ACID; WATER; DIHYDROXYALUMINUM AMINOACETATE ANHYDROUS; PROPYLENE GLYCOL; POLYACRYLIC ACID (250000 MW); SODIUM POLYACRYLATE (2500000 MW); TITANIUM DIOXIDE; MINERAL OIL; POLYSORBATE 80; GLYCERIN; EDETATE DISODIUM; POVIDONE K90; HYDROXYACETOPHENONE

Liuquanmiao, Lidocaine+Menthol Pain Relief Gel-Patch, Lidocaine 4%, Menthol 1%, 15 Patches

Active ingredients

Lidocaine 4% ...... Purpose: Topical anesthetic

Menthol 1% ...... Purpose: Topical analgesic

Purpose

Topical anesthetic (Lidocaine)

Topical analgesic (Menthol)

Uses

Temporarily relieves muscle soreness and minor joint pains in the wrist, knees, back, neck, hips, shoulders, elbows.

Warnings

For external use only

Do not use

- on wounds or damaged skin
- with a heating pad or device
- with other ointments, creams, sprays, or liniments
- if you are allergic to any ingredients of this product

When using this product

- use only as directed
- avoid contact with the eyes, mucous membranes or rashes
- do not bandage tightly

Stop use and ask a doctor if

- skin reactions such as redness, swelling, blistering or other discomfort occur
- symptoms persist for more than 7 days

If pregnant or breast-feeding,

ask a health professional before use.

KEEP OUT OF REACH OF CHILDREN.

If swallowed accidentally, get medical help or contact with Poison Control Center immediately.

Directions

Adult and Children above 12 years old:

- Clean and dry the affected area.
- Tear off the protective ﬁlm and apply the exposed part of the patch to the affected area.
- Carefully remove remaining film while pressing the patch firmly on the skin.
- Remove patch from the skin after at most 8-hour application.

Children under age of 12:Consult a doctor

Inactive ingredients

Dihydroxyaluminium Aminoacetate, Edetate Disodium, Glycerin, Hydroxyacetophenone, Kaolin, L(+)-Tartaric Acid, Mineral oil, Polysorbate 80, Polyacrylic Acid, Polyvinylpyrrolidone K90, Propylene Glycol, Sodium Polyacrylate, Titanium Dioxide, Water.

Questions or Comments:

supports@sumifunofficial.com